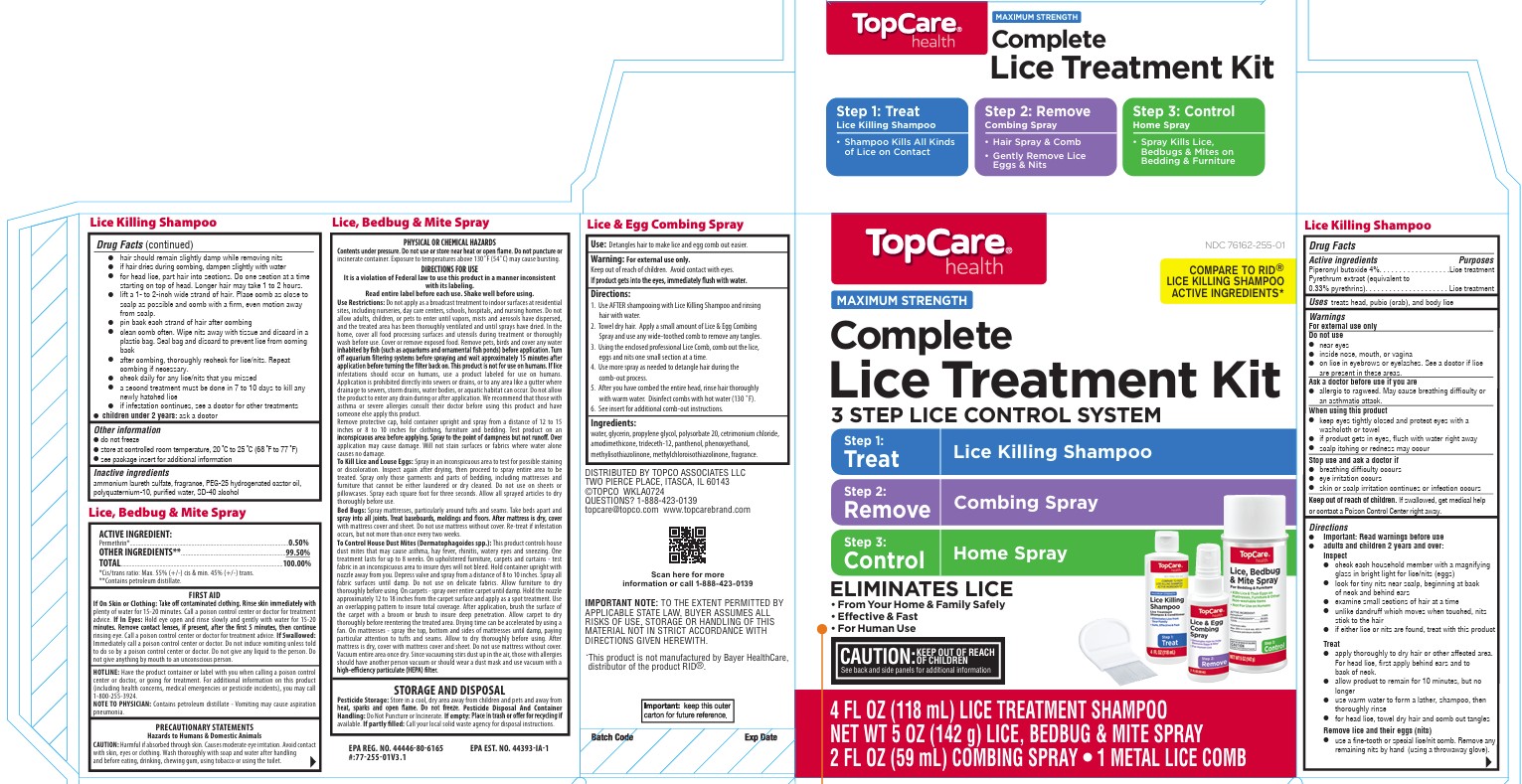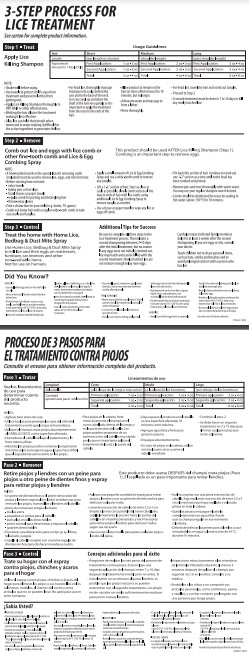 DRUG LABEL: Topcare Complete Lice Treatment Kit
NDC: 76162-255 | Form: KIT | Route: TOPICAL
Manufacturer: Topco Associates, LLC
Category: otc | Type: HUMAN OTC DRUG LABEL
Date: 20251111

ACTIVE INGREDIENTS: PIPERONYL BUTOXIDE 4 g/100 mL; PYRETHRUM EXTRACT 0.33 g/100 mL
INACTIVE INGREDIENTS: ALCOHOL; WATER; AMMONIUM LAURETH-2 SULFATE; POLYQUATERNIUM-10 (400 MPA.S AT 2%); PEG-25 HYDROGENATED CASTOR OIL

Topcare Lice Treatment Kit

Active ingredient

Piperonyl butoxide 4%
Pyrethrum extract (equivalent to 0.33% pyrethrins)

Uses

treats head, pubic (crab), and body lice

Purpose

Lice treatment

Warnings

For external use only

Do not use

near eyes
inside nose, mouth, or vagina
on lice in eyebrows or eyelashes. See a doctor if lice are present in these areas.

Ask a doctor before use if you are

allergic to ragweed. May cause breathing difficulty or an asthmatic attack.

When using this product

keep eyes tightly closed and protect eyes with a washcloth or towel
if product gets into eyes, flush with water right away
scalp itching or redness may occur

Stop use and ask a doctor if

breathing difficulty occurs
eye irritation occurs
skin or scalp irritation continues or infection occurs

Keep out of reach of children

If swallowed, get medical help or contact a Poison Control Center right away.

Directions

Important: Read warnings before use
Adults and children 2 years and over:

Inspect

check each household member with a magnifying glass in bright light for lice/nits (eggs)
look for tiny nits near scalp, beginning at back of neck and behind ears
examine small sections of hair at a time
unlike dandruff which moves when touched, nits stick to the hair
if either lice or nits are found, treat with this product

Treat

apply thoroughly to DRY HAIR or other affected area. For head lice, first apply behind ears and to back of neck.
allow product to remain for 10 minutes, but no longer
use warm water to form a lather, shampoo, then thoroughly rinse
for head lice, towel dry hair and comb out tangles

Remove lice and their eggs (nits)

use a fine-tooth or special lice/nit comb. Remove any remaining nits by hand (using a throw-away glove).
hair should remain slightly damp while removing nits
if hair dries during combing, dampen slightly with water
for head lice, part hair into sections. Do one section at a time starting on top of the head. Longer hair may take 1 to 2 hours.
lift a 1-to 2-inch wide strand of hair. Place comb as close to scalp as possible and comb with a firm, even motion away from scalp.
pin back each strand of hair after combing
clean comb often. Wipe nits away with tissue and discard in a plastic bag. Seal bag and discard to prevent lice from coming back.
after combing, thoroughly recheck for lice/nits. Repeat combing if necessary.
check daily for any lice/nits that you missed
a second treatment must be done in 7 to 10 days to kill any newly hatched lice
if infestation continues, see a doctor for other treatments
Children under 2 years: ask a doctor

Other information

do not freeze
store at controlled room temperature 20°-25°C (68°-77°F)
to report serious side effects due to the use of this product call (515) 276-1586

see package insert for additional information

Inactive ingredients

ammonium laureth sulfate, fragrance, PEG-25 hydrogenated castor oil, polyquaternium-10, purified water,SD-40 alcohol

Additional Information

Hair Length - Recommended Application for 1 Adult/Child

Short (ear length or shorter) Day 1: 1-2 oz; Day 7-10: 1-2oz; Total : 2-4oz

Medium (shoulder length) Day1: 2-3oz; Day 7-10: 2-3oz; Total: 4-6oz

Long (past shoulder length) Day 1: 3-4oz; Day 7-10: 3-4oz; Total: 6-8oz

Largo del cabello - Cantidad recomendada para 1 adulto/niño

Corto (hasta la oreja o más corto) Dia 1: 1-2oz; Dia7-10: 1-2oz; Total: 2-4oz

Medio (hasta el hombro) Dia1: 2-3oz; Dia 7-10: 2-3oz; Total: 4-6oz

Largo (más abajo del hombro) Dia 1: 3-4oz; Dia 7-10: 3-4oz; Total: 6-8oz

Important: keep this outer carton for future reference

Consumer Information

LICE KILLING SHAMPOO

For the treatment of Head Lice, Pubic (Crab) Lice and Body Lice

DIRECTIONS

Important: Read warnings before using this product. A second treatment must be done in 7-10 days to kill anu newly hatched lice eggs (nits)

Inspect

examine each household member with a magnifying glass in bright light for lice/eggs (nits)

look for tiny eggs (nits) near scalp, beginning at the back of neck and behind ears

examine small sections of hair

eggs (nits) stick to the hair

if either lice or eggs (nits) are found, treat with this product

Treat

apply thoroughly to dry hair or other affected area. For head lice, first apply behind ears and to back of neck

allow product to remain for 10 minutes but no longer

use warm water to form a lather, shampoo, then thoroughly rinse

for head lice, towel dry hair and comb out tangles

To Remove Lice and Their Eggs (Nits)

use a special lice/nit or fine-toothed comb (included). Remove any remaining eggs (nits) by hand, using a throwaway glove

hair should remain slightly damp while removing eggs (nits)

if hair dries during combing, dampen slightly with water

for head lice, part hair into sections. Do one section at a time starting on top of the head. Longer hair may take 1 to 2 hours

lift a 1- to 2-inch wide strand of hair. Place comb firm, even motion away from scalp

pin back each strand of hair after combing

clean comb often. Wipe eggs (nits) away with tissue and discard in a plastic bag. Seal bag and discard to prevent lice from coming back

after combing, thoroughly recheck for lice/eggs (nits). Repeat combing if necessary

check daily for any lice/eggs (nits) that you missed

a second treatment must be done within 7 to 10 days to kill any newly hatched lice/eggs (nits)

if infestation continues, see a doctor for other treatments

1. HEAD LICE

head lice lay small white eggs (nits) on the hair shaft close to the scalp

eggs (nits) are most easily found on the back of the neck or behind the ears

disinfect hats, hair ribbons, scarves, coats, towels and bed linens by machine washing in hot water [above 54 C (130 F)], then using the hottest dryer setting for at least 20 minutes

items that cannot be washed, dry cleaned or stored may be sprayed with a product designed for this purpose

soak all combs and brushes in hot water [above 54 C (130 F)] for at least 10 minutes

vacuum all carpets, mattresses, upholstered furniture, and car seats that may have been used by affected people

2. PUBIC (CRAB) LICE

pubic (crab) lice may be contracted by sexual contact

sexual partners should be treated simultaneously to avoid reinfestation

lice are very small and look like brown or grey dots on the skin

pubic (crab) lice usually cause intense itching and lay small white eggs (nits) on the hair shaft generally close to the skin surface

pubic (crab) lice may be present on the short hairs of the groin, thighs, trunk, and underarms, -and occasionally on the beard, eyelids, and mustache

disinfect underwear by machine washing in hot water [above 54 C (130 F)], then using the hottest dryer setting for at least 20 minutes

3. BODY LICE

body lice and their eggs (nits) are generally found in the seams of clothing, particularly in the waistline and armpit areas

body lice feed on skin then return to clothing to lay their eggs (nits)

disinfect clothing by machine washing in hot water [above 54 C (130 F)], then using the hottest dryer setting for at least 20 mintues

do not seal clothing in a plastic bag because eggs (nits) can remain dormant for up to 30 days

Save this insert for future reference

SHAKE WELL BEFORE USING

CHAMPÚ PARA MATAR PIOJOS

Para el tratamiento de piojos de cabeza, piojos púbicos (ladillas) y piojos del cuerpo

Para uso externo solamente.

No lo use

cerca de los ojos

dentro de la nariz, boca o vagina

para piojos en las cejas o pestañas. Consulte a un doctor si hay piojos en estas áreas.

Pregúntele a un doctor antes de usarlo si

es alérgico a la ambrosía. Puede provocar dificultades para respirar o un ataque asmático.

Cuando use este producto

mantenga los ojos bien cerrados y protéjalos con una toallita o toalla

si el producto entra en los ojos, enjuáguese inmediatamente con agua

puede experimentar picazón o enrojecimiento del cuero cabelludo.

Deje de usarlo y consulte a un doctor si

tiene dificultad para respirar

presenta irritación de los ojos

prevalece la irritación de la piel o el cuero cabelludo o se presenta una infección.

Si está embarazada o lactando, antes de usarlo pregunte a un profesional médico. Manténgalo fuera del alcance de los niños. Si e traga, obtenga ayuda médica o póngase en contacto de inmediato con el Centro de Control de Envenenamientos

INSTRUCCIONES

IMPORTANTE: LEA LAS ADVERTENCIAS ANTES DE USAR ESTA PRODUCTO. UN SEGUNDO TRATAMIENTO DEBE SER REALIZADO ENTRE 7 Y 10 DIAS PARA ELIMINAR LA REPRODUCCIÓN DE NUEVOS PIOJOS Y HUEVECILLOS (LIENDRES).

Inspeccione

Examine a cada uno de los integrantes de la familia bajo luz brillante con una lupa en busca de piojos o huevecillos (liendres)

usque los huevecillos (liendres) en el cabello, comenzando en la parte posterior del cuello y detrás de las orejas

examine áreas pequeñas del cabello

a diferencia de la caspa, la cual se mueve al tocarla, los huevecillos (liendres) permanecen adheridos al cabello

si encuentra piojos o huevecillos (liendres) trate las áreas afectadas con este producto.

Tratamiento

aplique sobre todo el cabello seco u otras áreas afectadas. Para liendres de cabeza primero aplique detrás de las orejas y en la parte posterior del cuello

deje el producto durante 10 minutos, pero no se exceda del tiempo sugerido

use agua tibia para formar espuma, lave con champú y luego enjuague muy bien

para liendres de cabeza, seque el cabello con una toalla y desenrede con un peine.

Para eliminar los piojos y sus huevecillos (liendres)

use un peine de dientes finos o un peine especial para piojos y liendres. Remueva todos las huevecillos (liendres) restantes a ano usando guantes desechables

el pelo debe permanecer húmedo mientras se remueven los huevecillos (liendres)

si el pelo se seca mientras es peinado, humedézcalo con agua

para liendres de cabeza, divida el pelo en secciones. Revise una sección a la vez comenzando por la parte de arriba de la cabeza. Si tiene pelo largo le puede tomar de 1 o 2 horas

levante mechones de una pulgada de ancho. Ponga el peine lo más cerca posible del cuero cabelludo y peine con movimentos parejos y firmes

sujete cada mechón de pelo después de peinar limpie el peine con frecuencia. Limpie los huevecillos (liendres) con un papel toalla y tirvelas en una bolsa plástica. Cierre la bolsa y tirela para prevenir que los piojos vuelvan a aparecer

después de peinar, vuelva a revisar para ver si encuentra piojos o huevecillos (liendres). Si fuera necesario repita el procedimiento

revise a diario para ver si aparece algún piojo o huevecillo (liendres)

se debe efectuar un segundo tratamiento a los 7 a 10 días para matar los huevecillos nuevos (liendres)

si la plaga continua se debe consultar con el doctor para hacer otros tratamiento.

Otra Información

no lo congele

protéjalo del calor excesivo

vea la información adicional en el anexo del paquete

Ingredientes Inactivos ,lauril sulfato de amonio, lauril sulfato de amonio, fragancia, PEG-25 aceite de ricino hidrogenado, policuaternio-10, alcohol desnaturalizado SD 40-B, agua

1. PIOJOS DE LA CABEZA

Los piojos de cabeza ponen huevos blancos (liendres) en los hebra del cabello cerca del cuero cabelludo. Las liendres son fáciles de encontrar en la parte posterior del cuello o detrás de las orejas.

Desinfecte los sombreros, cintas para el cabello, bufandas, abrigos, toallas y sábanas lavándolos en lavadora con agua caliente [a una temperatura de más de 54 C (130 F)], y luego séquelos en la secadora a la temperatura más alta durante un mínimo de 20 minutos.

Los artículos que no pueden ser lavados (cubrecamas, frizas, almohadas, juguetes de peluche, etc.) deben ser limpiados en seco o deben ser sellados en bolsas plásticas por 4 semanas, después sacados a la intemperie y sacudidos enérgicamente antes de ser usados otra vez.

artículos que no pueden ser lavados, limpiados en seco o guardados deben ser rociados con productos designados para este fin.

Sumerja todos los peines y cepillos en agua caliente, [por más de 54 C (130 F)] por lo menos por 10 minutos.

Limpie las alfombras, colchones, muebles tapizados y asientos del carro que pueden haber sido usados por personas infectadas.

2. PIOJOS PÚBICOS (LADILLAS)

Los piojos púbicos (ladillas) pueden adquirirse por contacto sexual.

Compañeros sexuales deben ser tratados simultáneamente para evitar contagios.

Los piojos son muy pequeños y parecen puntos cafés o grises sobre la piel.

Piojos púbicos producen picazón muy intensa y ponen huevos muy pequeños (liendres) en los mechones de pelo cerca de la superficie de la piel.

Los piojos púbicos pueden encontrarse en los pelos cortos de las ingles, muslos, tórax y axilas, y ocasionalmente pueden encontrarse en la barba, párpados y bigote.

Desinfecte la ropa interior lavándola en lavadora con agua caliente [a una temperatura de más de 54 C (130 F)], y secándola luego en la secadora a la temperatura más alta durante un mínimo de 20 minutos.

3. PIOJOS DE CUERPO

Los piojos de cuerpo (y sus liendres) son generalmente encontrados en los dobladillos de la ropa, particularmente en el elástico de la cintura o en la zona de la axila.

Las liendres del cuerpo se alimentan de la piel y luego retornan a la ropa para depositar sus huevos (liendres).

Desinfecte la ropa lavándola en la lavadora en agua caliente [a una temperatura de más de 54 C (130 F)], y luego use el ciclo más caliente de la secadora por más caliente de la secadora por más de 20 minutos.

No selle la ropa dentro de una bolsa de plástico debido a que los huevecillos (liendres) pueden permanecer en estado inactivo durante un período de hasta 30 días.

Guarde las instrucciones para futuras referencias.

AGÍTESE MUY BIEN ANTES DE USAR

Principal Display Panel

TopCare

Maximum Strength

Complete Lice Treatment Kit

Compare to RID® Lice Killing Shampoo Active Ingredients

Eliminates Lice from Your Home & Family

Shampoo 4 fl oz (118 mL)

Lice Spray Net Wt. 5 oz (142 g)

Combing Spray 2 fl oz (59 mL)

1 Metal Lice Comb

CAUTION: KEEP OUT OF REACH OF CHILDREN
See back and side panels for additional information